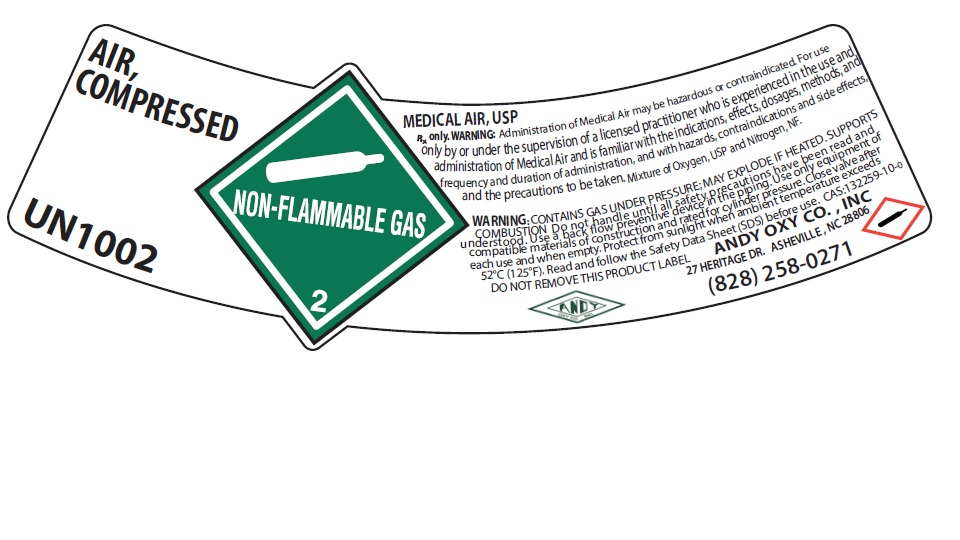 DRUG LABEL: Air
NDC: 50063-004 | Form: GAS
Manufacturer: Andy-Oxy Co., Inc.
Category: prescription | Type: HUMAN PRESCRIPTION DRUG LABEL
Date: 20251030

ACTIVE INGREDIENTS: OXYGEN 210 mL/1 L

air

PACKAGE LABEL

AIR, COMPRESSED

UN1002

MEDICAL AIR, USP

Rx only. WARNING: Administration of Medical Air may be hazardous or contraindicated. For use only by or under the supervision of a licensed practitioner who is experienced in the use and administration of Medical Air and is familiar with the indications, effects, dosages, methods, and frequency and duration of administration, and with hazards, contraindications and side effects, and the precautions to be taken. Mixture of Oxygen, USP and Nitrogen, NF.

WARNING: CONTAINS GAS UNDER PRESSURE; MAY EXPLODE IF HEATED. SUPPORTS COMBUSTION. Do not handle until all safety precautions have been read and understood. Use a back flow preventive device in the piping. Use only equipment of compatible materials of construction and rated for cylinder pressure. Close valve after each use and when empty. Protect from sunlight when ambient temperature exceeds 52 C (125 F). Read and follow the Safety Data Sheet (SDS) before use. CAS: 132259-10-0

DO NOT REMOVE THIS PRODUCT LABEL

ANDY OXY CO., INC

27 HERITAGE DR. ASHEVILLE, NC 28806

(828) 258-0271